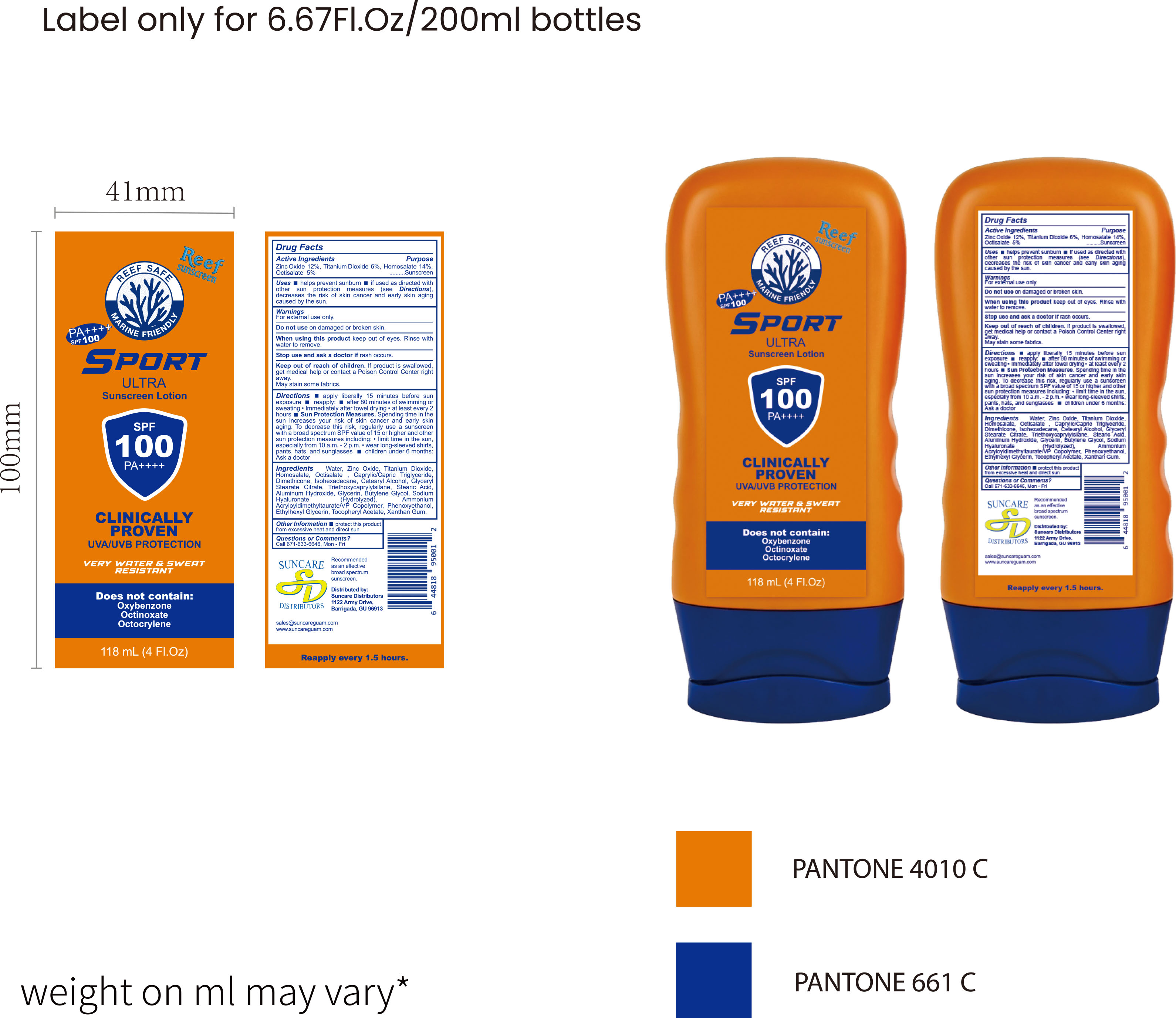 DRUG LABEL: Sunscreen Lotion118ml
NDC: 84938-011 | Form: LOTION
Manufacturer: Foshan Sugar Max Cosmetics CO.,Ltd
Category: otc | Type: HUMAN OTC DRUG LABEL
Date: 20251217

ACTIVE INGREDIENTS: TITANIUM DIOXIDE 0.06 g/1 mL; HOMOSALATE 0.14 g/1 mL; OCTISALATE 0.05 g/1 mL; ZINC OXIDE 0.12 g/1 mL
INACTIVE INGREDIENTS: TRIETHOXYCAPRYLYLSILANE; ALUMINUM HYDROXIDE; XANTHAN GUM; CETEARYL ALCOHOL; STEARIC ACID; ISOHEXADECANE; .ALPHA.-TOCOPHEROL ACETATE; GLYCERYL STEARATE CITRATE; SODIUM HYALURONATE; PHENOXYETHANOL; ETHYLHEXYLGLYCERIN; DIMETHICONE; BUTYLENE GLYCOL; GLYCERIN; AMMONIUM ACRYLOYLDIMETHYLTAURATE/VP COPOLYMER; CAPRYLIC/CAPRIC TRIGLYCERIDE; AQUA

84938-011 Sunscreen Lotion

ACTIVE INGREDIENT

Zinc Oxide 12%,Titanium Dioxide 6%, Homosalate 14%,Octisalate 5%

PURPOSE

Sunscreen

INDICATIONS AND USAGE

Uses helps prevent sunburn if used as directed with other sun protection measures(see Directions),decreases the risk of skin cancer and early skin aging caused by the sun.

WARNINGS

For external use only.

Do not use on damaged or broken skin.

When using this product keep out of eyes. Rinse with water to remove.

Stop use and ask a doctor if rash occurs

Keep out of reach of children. lf product is swallowed get medical help or contact a Poison Control Center right away.
May stain some fabrics.

DOSAGE AND ADMINISTRATION

Directions apply liberally 15 minutes before sun exposure reapply: after 80 minutes of swimming or sweating"lmmediately after towel drying " at least every 2 hours Sun Protection Measures. Spending time in the sun increases your risk of skin cancer and early skinaging. To decrease this risk, regularly use a sunscreen with a broad spectrum SPF value of 15 or higher and other sun protection measures including:" limit time in the sun,especially from 10 a.m.-2 p.m. wear long-sleeved shirtspants, hats,and sunglasses children under 6 months.Ask a doctor

INACTIVE INGREDIENT

Aqua (Water)
Caprylic/Capric Triglyceride
Dimethicone
Isohexadecane
Cetearyl Alcohol
Glyceryl Stearate Citrate
Triethoxycaprylylsilane
Stearic Acid
Aluminum Hydroxide
Glycerin
Butylene Glycol
Sodium Hyaluronate (Hydrolyzed)
Ammonium Acryloyldimethyltaurate/VP Copolymer
Phenoxyethanol
Ethylhexyl Glycerin
Tocopheryl Acetate
Xanthan Gum